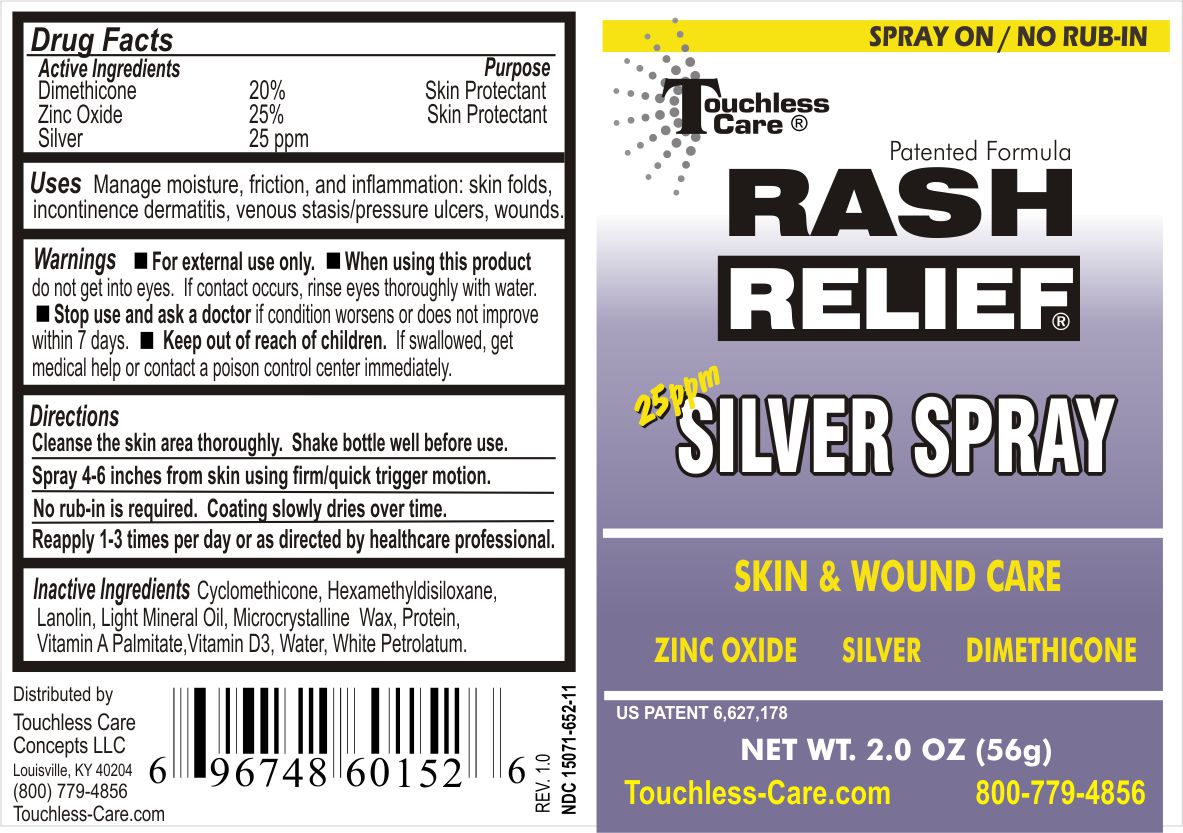 DRUG LABEL: Rash Relief Silver 
NDC: 15071-652 | Form: LIQUID
Manufacturer: Touchless Care Concepts LLC
Category: otc | Type: HUMAN OTC DRUG LABEL
Date: 20111116

ACTIVE INGREDIENTS: Dimethicone 20 g/100 g; Zinc Oxide 25 g/100 g
INACTIVE INGREDIENTS: Mineral Oil; Cyclomethicone; Lanolin; Microcrystalline Wax; Hexamethyldisiloxane; Water; Cholecalciferol; Vitamin A Palmitate; Petrolatum; Casein; Silver

RASH RELIEF SILVER SPRAY

Active Ingredients

Dimethicone 20%

Petrolatum 25%

Silver 25 ppm

Purpose

Skin Protectant.

Warnings

- For external use only.

- When using this product do not get into eyes. If contact occurs, rinse eyes thoroughly with water. For external use only.

- Stop use and ask a doctor if condition worsens or does not improve in 7 days.

Directions

- Cleanse the skin area thoroughly.

- Shake bottle well before use.

- Spray 4-6 inches from skin using firm/quick trigger motion. No rub-in is required. Coating slowly dries over time.

- Reapply 1-3 times per day or as directed by health professional.

Inactive Ingredients

Cyclomethicone, Hexamethyldisiloxane, Lanolin, Light Mineral Oil, Microcrystalline Wax, Protein, Vitamin A Palmitate, Vitamin D3, Water, White Petrolatum

INDICATIONS AND USAGE

Manage moisture, friction, and inflammation: skin folds, incontinence dermatitis, venous stasis/pressure ulcers, wounds

Keep out of reach of children. If swallowed, get medical help or contact a local poison control center immediately.

PACKAGE LABEL

Enter section text here